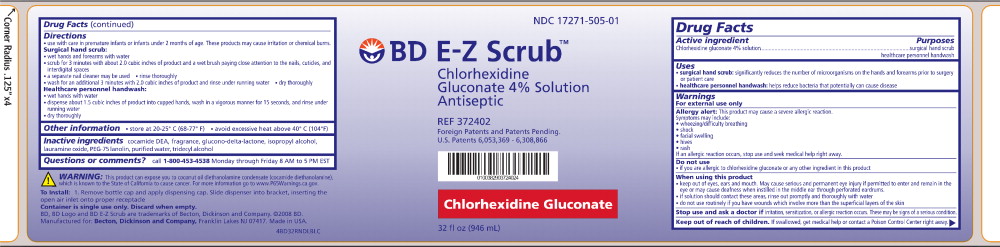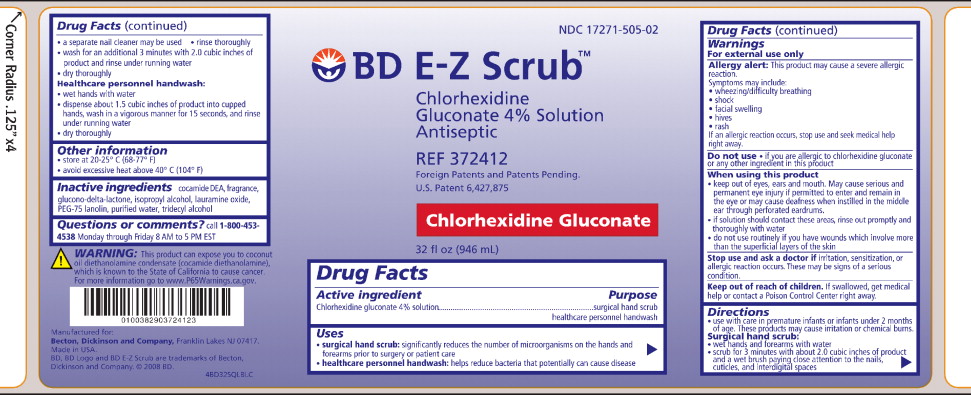 DRUG LABEL: BD E-Z Scrub
NDC: 17271-505 | Form: SOLUTION
Manufacturer: Becton Dickinson and Company
Category: otc | Type: HUMAN OTC DRUG LABEL
Date: 20241212

ACTIVE INGREDIENTS: CHLORHEXIDINE GLUCONATE 40 g/1000 mL
INACTIVE INGREDIENTS: GLUCONOLACTONE; ISOPROPYL ALCOHOL; LAURAMINE OXIDE; PEG-75 LANOLIN; COCO DIETHANOLAMIDE; WATER; TRIDECYL ALCOHOL

Drug Facts

Active Ingredient

Chlorhexidine gluconate 4% solution

Purposes

surgical hand scrub

healthcare personnel handwash

Uses

- surgical hand scrub: significantly reduces the number of microorganisms on the hands and forearms prior to surgery or patient care
- healthcare personnel handwash: helps reduce bacteria that potentially can cause disease

Warnings

For external use only

Allergy alert: This product may cause a severe allergic reaction.

Symptoms may include:

- wheezing/difficulty breathing
- shock
- facial swelling
- hives
- rash

If an allergic reaction occurs, stop use and seek medical help right away.

Do not use

if you are allergic to chlorhexidine gluconate or any other ingredient in this product

When using this product

- keep out of eyes, ears and mouth. May cause serious and permanent eye injury if permitted to enter and remain in the eye or may cause deafness when instilled in the middle ear through perforated eardrums.
- if solution should contact these areas, rinse out promptly and thoroughly with water
- do not use routinely if you have wounds which involve more than the superficial layers of the skin

Stop use and ask a doctor if irritation, sensitization, or allergic reaction occurs. These may be signs of a serious condition.

Keep out of reach of children. If swallowed, get medical help or contact a Poison Control Center right away.

Directions

- use with care in premature infants or infants under 2 months of age. These products may cause irritation or chemical burns.

Surgical hand scrub:

- wet hands and forearms with water
- scrub for 3 minutes with about 2.0 cubic inches of product and a wet brush paying close attention to the nails, cuticles, and interdigital spaces
- a separate nail cleaner may be used
- rinse thoroughly
- wash for an additional 3 minutes with 2.0 cubic inches of product and rinse under running water
- dry thoroughly

Healthcare personnel handwash:

- wet hands with water
- dispense about 1.5 cubic inches of product into cupped hands, wash in a vigorous manner for 15 seconds, and rinse under running water
- dry thoroughly

Other information

- store at 20-25° C (68-77° F)
- avoid excessive heat above 40° C (104° F)

Inactive ingredients

cocamide DEA, fragrance, glucono-delta-lactone, isopropyl alcohol, lauramine oxide, PEG-75 lanolin, purified water, tridecyl alcohol

Questions or comments?

call 1-800-453-4538

Monday through Friday 8 AM to 5 PM EST

Principal Display Panel – Box Label

NDC 17271-505-01

BD E-Z Scrub™

Chlorhexidine

Gluconate 4% Solution

Antiseptic

REF 372402

Foreign Patents and Patents Pending.

U.S. Patents 6,053,369 - 6,308,866

Chlorhexidine Gluconate

32 fl oz (946 mL)

Principal Display Panel – Box Label

NDC 17271-505-02

BD E-Z Scrub™

Chlorhexidine

Gluconate 4% Solution

Antiseptic

REF 372412

Foreign Patents and Patents Pending.

U.S. Patents 6,427,875

Chlorhexidine Gluconate

32 fl oz (946 mL)